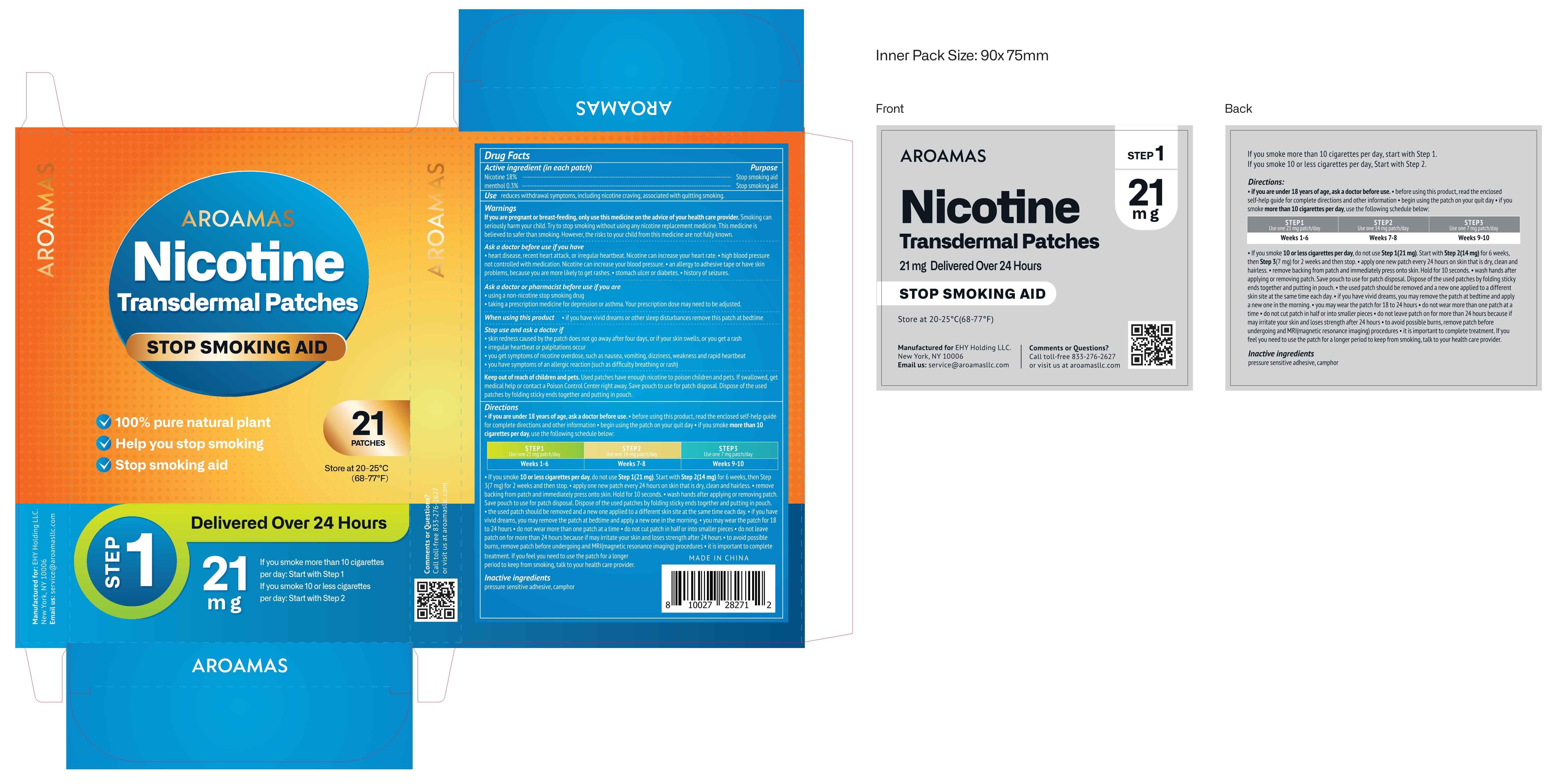 DRUG LABEL: Nicotine Transdermal Patches
NDC: 81799-001 | Form: PATCH
Manufacturer: Ehy Holdings LLC
Category: otc | Type: HUMAN OTC DRUG LABEL
Date: 20230109

ACTIVE INGREDIENTS: MENTHOL 0.3 mg/100 mg; NICOTINE 18 mg/100 mg
INACTIVE INGREDIENTS: CHRYSANTHEMUM INDICUM FLOWER; CLOVE; CODONOPSIS PILOSULA WHOLE; TOBACCO LEAF

81799-001
Nicotine Transdermal Patches

Active Ingredient(s)

Nicotine 18%
menthol 0.3%

Purpose

Stop smoking aid

Use

reduces withdrawal symptoms, including nicotine craving, associated with quitting smoking

Warnings

If you are pregnant or breast-feeding, only use this medicine on the advice of your healthcare provider.Smoking can seriously harm your child.Try to stop smoking without using any nicotine replacement medicine.This medicine is believed to safer than smoking.However, the risks to your child from this medicine are not full known.

Ask a doctor before use if you have
*heart disease, recent heartattack, or irregular heartbeat.Nicotine can increase your heartrate.
*high blood pressure not controlled with medication.Nicotine can increase your blood pressure.
*an allergy to adhesive tape or have skin problems, because you are more likely to get rashes.
*stomach ulcer or diabetes.
*history of seizures.

Ask a doctor or pharmacist before use if you are
*using an on-nicotine stop smoking drug
*taking a prescription medicine for depression or asthma.Your prescription dose may need to be adjusted

Do not use

*do not wear more than one patch at a time
*do not cut patch in half or into smaller pieces
*do not leave patch on for more than 24 hours because if may irritate your skin and loses strength after 24 hours

When using this product
*if you have vivid dreams or other sleep disturbances remove this patch at bedtime

Stop use and ask a doctor if
*skin redness caused by the patch does not go away after four days, or if your skins wells, or you get arash
*irregular heartbeat or palpitations occur
*you get symptoms of nicotine overdose, such as nausea, vomiting, dizziness, weakness and rapid heartbeat
*you have symptoms of an allergic reaction(such as difficulty breathing or rash)

Keep out of reach of children and pets.
Used patches have enough nicotine to poison children and pets.If swallowed, get medical help or contact a Poison Control Center right away.Save pouch to use for patch di posal.Dispose of the used patches by folding sticky ends together and putting in pouch.

Directions

*if you are under 18 years of age, ask a doctor before use.*before using this product, read the enclosed self-help guide for complete directions and other information
*begin using the patch on your quit day
*if you smoke more than 10 cigarettes per day, use the following schedule below：

STEP 1 | STEP 2 | STEP 3
Use one 21mg patch/day | Use one 14mg patch/day | Use one 7mg patch/day
Weeks 1-6 | Weeks 7-8 | Weeks 9-10

*If you smoke 10 or less cigarettes per day, do not use Step 1(21mg) .Start with Step 2(14mg) for 6 weeks, then Step 3(7mg) for 2 weeks and then stop.
*apply one new patch every 24 hours on skin that is dry, clean and hairless.
*remove backing from patch and immed ately press on to skin.Hold for 10 seconds..wash hands after applying or removing patch.
Save pouch to use for patch disposal.Dispose of the used patches by folding sticky ends together and putting in pouch.
*the used patch should be removed and a new one applied to a different skin site at the sametime each day.
*if you have vivid dreams, you may remove the patch at bedtime and apply a new one in the morning.
*you may wear the patch for 18 to 24 hours
*do not wear more than one patch at a time
*do not cut patch in half or into smaller pieces
*do not leave patch on for more than 24 hours because if may irritate your skin and loses strength after 24 hours
*to avoid possible burns, remove patch before undergoing and MR(magnetic resonance imaging) procedures
*it is important to complete treatment.If you feel you need to use the patch for a longer period to keep from smoking, talk to your healthcare provider.

Other information

If you smoke more than 10 cigarettes per day, start with Step 1.
lfyousmoke10or less cigarettes per day, Start with Step 2.

Inactive ingredients

codonopsis pilosula, chrysanthemum, clove, natural tobacco

Package Label - Principal Display Panel

21 PATCH in 1 BOX (81799-001-00) > 21 mg in 1 PATCH